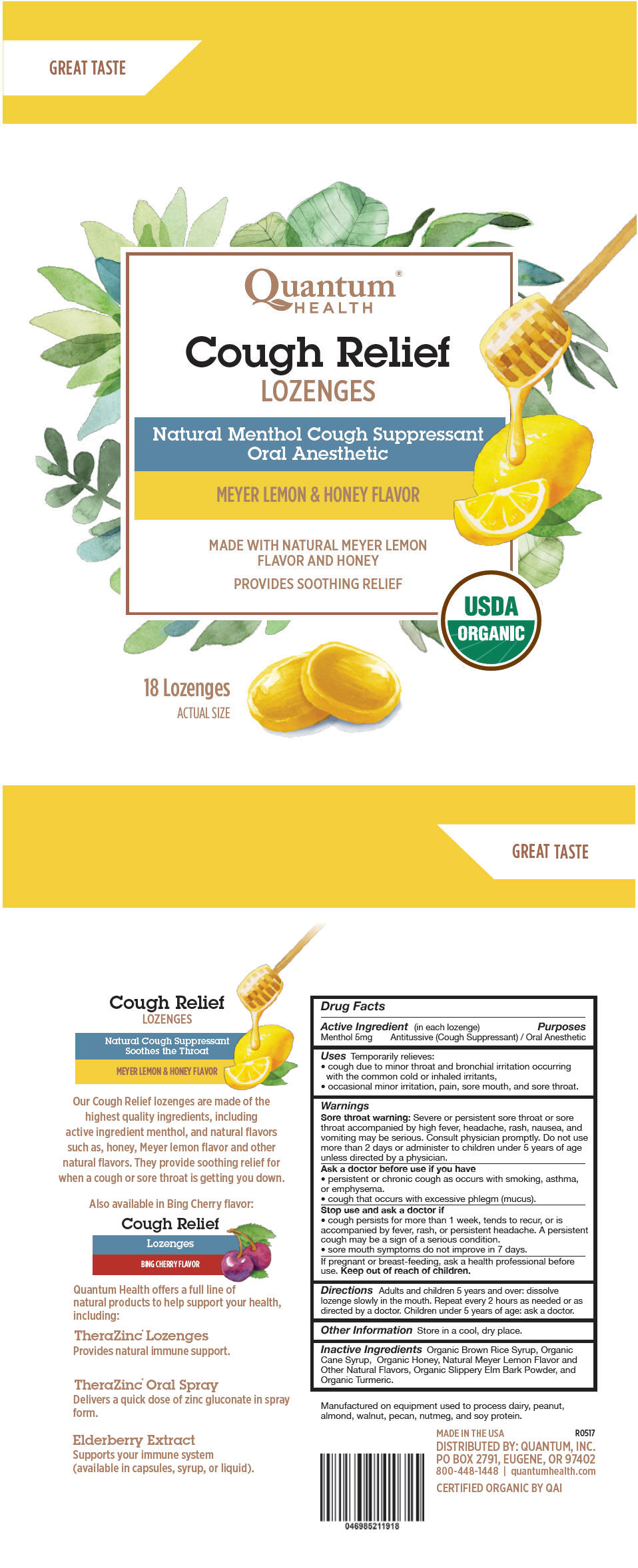 DRUG LABEL: Quantum Health Meyer Lemon and Honey Flavor
NDC: 70084-605 | Form: LOZENGE
Manufacturer: Quantum, Inc.
Category: otc | Type: HUMAN OTC DRUG LABEL
Date: 20251020

ACTIVE INGREDIENTS: MENTHOL, UNSPECIFIED FORM 5 mg/1 1
INACTIVE INGREDIENTS: BROWN RICE; SUCROSE; HONEY; ULMUS RUBRA BARK; TURMERIC

Quantum®Health Meyer Lemon & Honey Flavor Lozenges

Drug Facts

Active Ingredient (in each lozenge)

Menthol 5mg

Purposes

Antitussive (Cough Suppressant) / Oral Anesthetic

Uses

Temporarily relieves:

- cough due to minor throat and bronchial irritation occurring with the common cold or inhaled irritants,
- occasional minor irritation, pain, sore mouth, and sore throat.

Warnings

Sore throat warning

Severe or persistent sore throat or sore throat accompanied by high fever, headache, rash, nausea, and vomiting may be serious. Consult physician promptly. Do not use more than 2 days or administer to children under 5 years of age unless directed by a physician.

Ask a doctor before use if you have

- persistent or chronic cough as occurs with smoking, asthma, or emphysema.
- cough that occurs with excessive phlegm (mucus).

Stop use and ask a doctor if

- cough persists for more than 1 week, tends to recur, or is accompanied by fever, rash, or persistent headache. A persistent cough may be a sign of a serious condition.
- sore mouth symptoms do not improve in 7 days.

PREGNANCY OR BREAST FEEDING

If pregnant or breast-feeding, ask a health professional before use.

Keep out of reach of children.

Directions

Adults and children 5 years and over: dissolve lozenge slowly in the mouth. Repeat every 2 hours as needed or as directed by a doctor. Children under 5 years of age: ask a doctor.

Other Information

Store in a cool, dry place.

Inactive Ingredients

Organic Brown Rice Syrup, Organic Cane Syrup, Organic Honey, Natural Meyer Lemon Flavor and Other Natural Flavors, Organic Slippery Elm Bark Powder, and Organic Turmeric.

DISTRIBUTED BY: QUANTUM, INC.
PO BOX 2791, EUGENE, OR 97402

PRINCIPAL DISPLAY PANEL - 18 Lozenge Bag

GREAT TASTE

Quantum®
HEALTH

Cough Relief
LOZENGES

Natural Menthol Cough Suppressant
Oral Anesthetic

MEYER LEMON & HONEY FLAVOR

MADE WITH NATURAL MEYER LEMON
FLAVOR AND HONEY

PROVIDES SOOTHING RELIEF

USDA
ORGANIC

18 Lozenges

ACTUAL SIZE